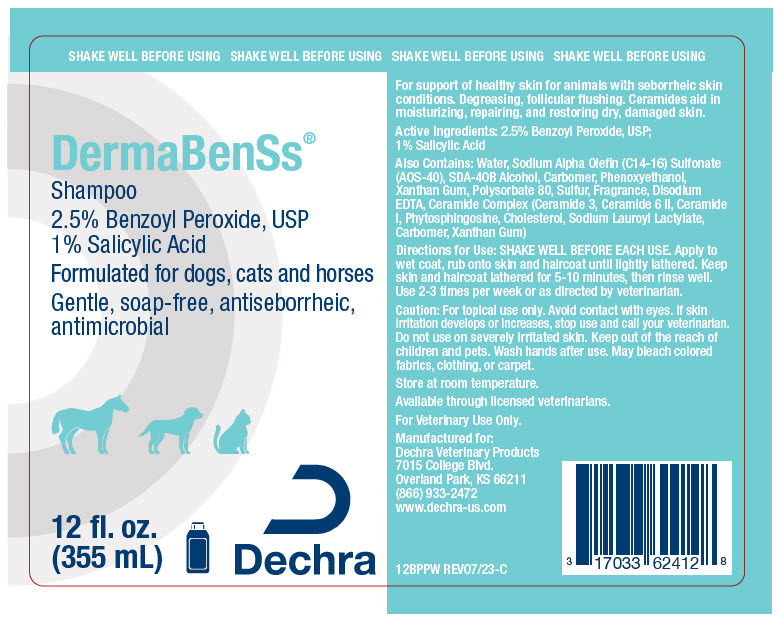 DRUG LABEL: DermaBenSs
NDC: 17033-624 | Form: SHAMPOO, SUSPENSION
Manufacturer: Dechra Veterinary Products
Category: animal | Type: OTC ANIMAL DRUG LABEL
Date: 20230913

ACTIVE INGREDIENTS: BENZOYL PEROXIDE 25 mg/1 mL; SALICYLIC ACID 10 mg/1 mL
INACTIVE INGREDIENTS: Alcohol; Ceramide AP

DermaBenSs® Shampoo

VETERINARY INDICATIONS

For support of healthy skin for animals with seborrheic skin conditions. Degreasing, follicular flushing. Ceramides aid in moisturizing, repairing, and restoring dry, damaged skin.

DESCRIPTION

Active Ingredients: 2.5% Benzoyl Peroxide, USP; 1% Salicylic Acid

Also Contains: Water, Sodium Alpha Olefin (C14-16) Sulfonate (AOS-40), SDA-40B Alcohol, Carbomer, Phenoxyethanol, Xanthan Gum, Polysorbate 80, Sulfur, Fragrance, Disodium EDTA, Ceramide Complex (Ceramide 3, Ceramide 6 II, Ceramide I, Phytosphingosine, Cholesterol, Sodium Lauroyl Lactylate, Carbomer, Xanthan Gum)

DOSAGE AND ADMINISTRATION

Directions for Use: SHAKE WELL BEFORE EACH USE. Apply to wet coat, rub onto skin and haircoat until lightly lathered. Keep skin and haircoat lathered for 5-10 minutes, then rinse well. Use 2-3 times per week or as directed by veterinarian.

SAFE HANDLING WARNING

Caution: For topical use only. Avoid contact with eyes. If skin irritation develops or increases, stop use and call your veterinarian. Do not use on severely irritated skin. Keep out of the reach of children and pets. Wash hands after use. May bleach colored fabrics, clothing, or carpet.

STORAGE AND HANDLING

Store at room temperature.

Available through licensed veterinarians.

For Veterinary Use Only.

Manufactured for:
Dechra Veterinary Products
7015 College Blvd.
Overland Park, KS 66211
(866) 933-2472
www.dechra-us.com

12BPPW REV07/23-C

PRINCIPAL DISPLAY PANEL - 355 mL Bottle Label

SHAKE WELL BEFORE USING

DermaBenSs®

Shampoo

2.5% Benzoyl Peroxide, USP
1% Salicylic Acid

Formulated for dogs, cats and horses
Gentle, soap-free, antiseborrheic,
antimicrobial

12 fl. oz.
(355 mL)

Dechra